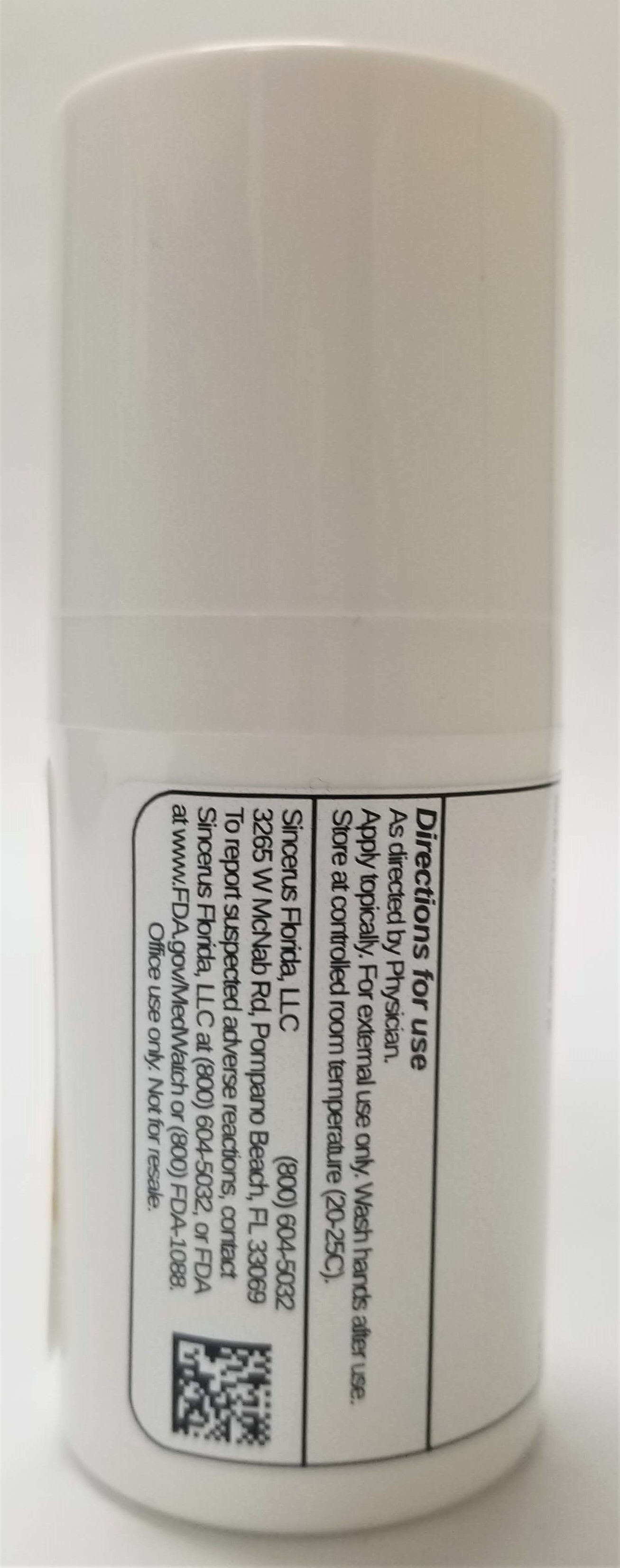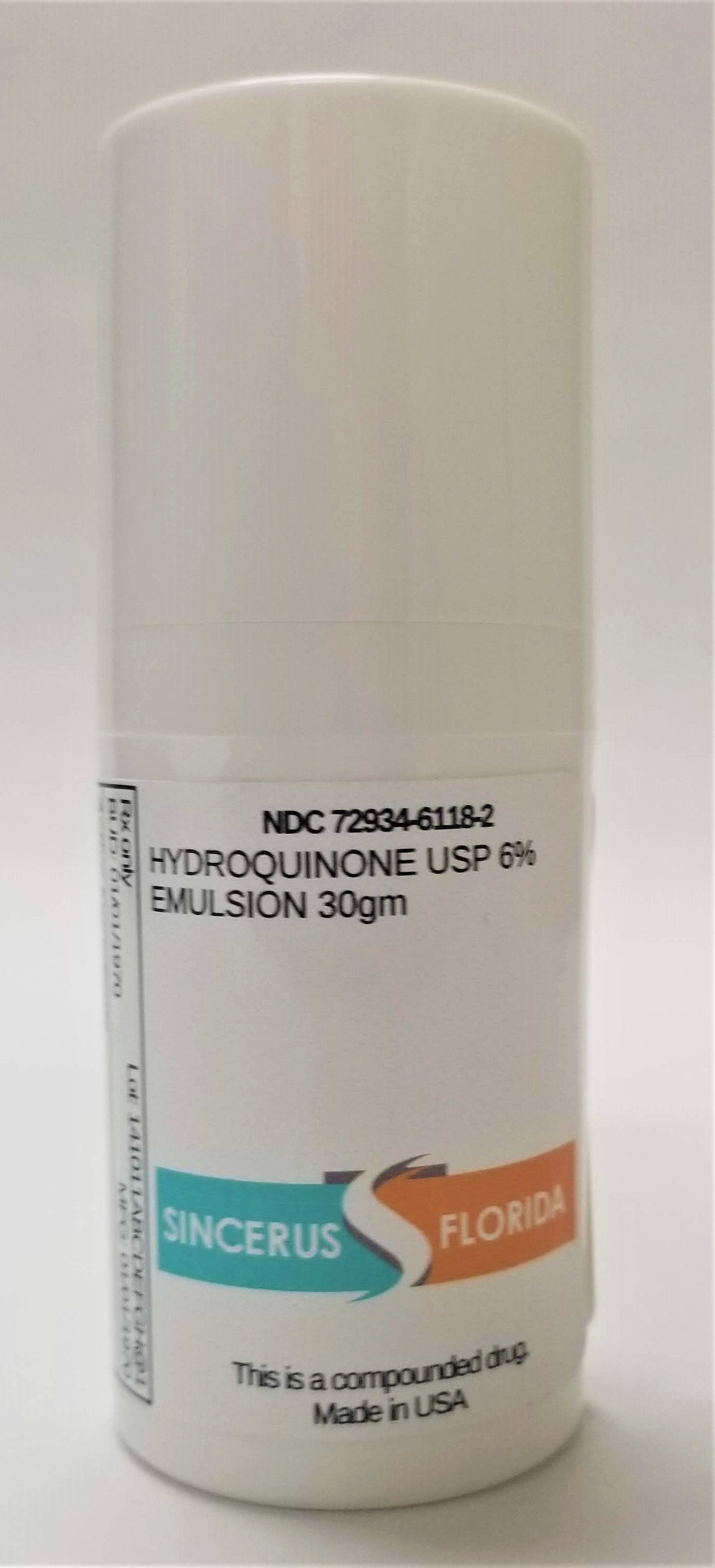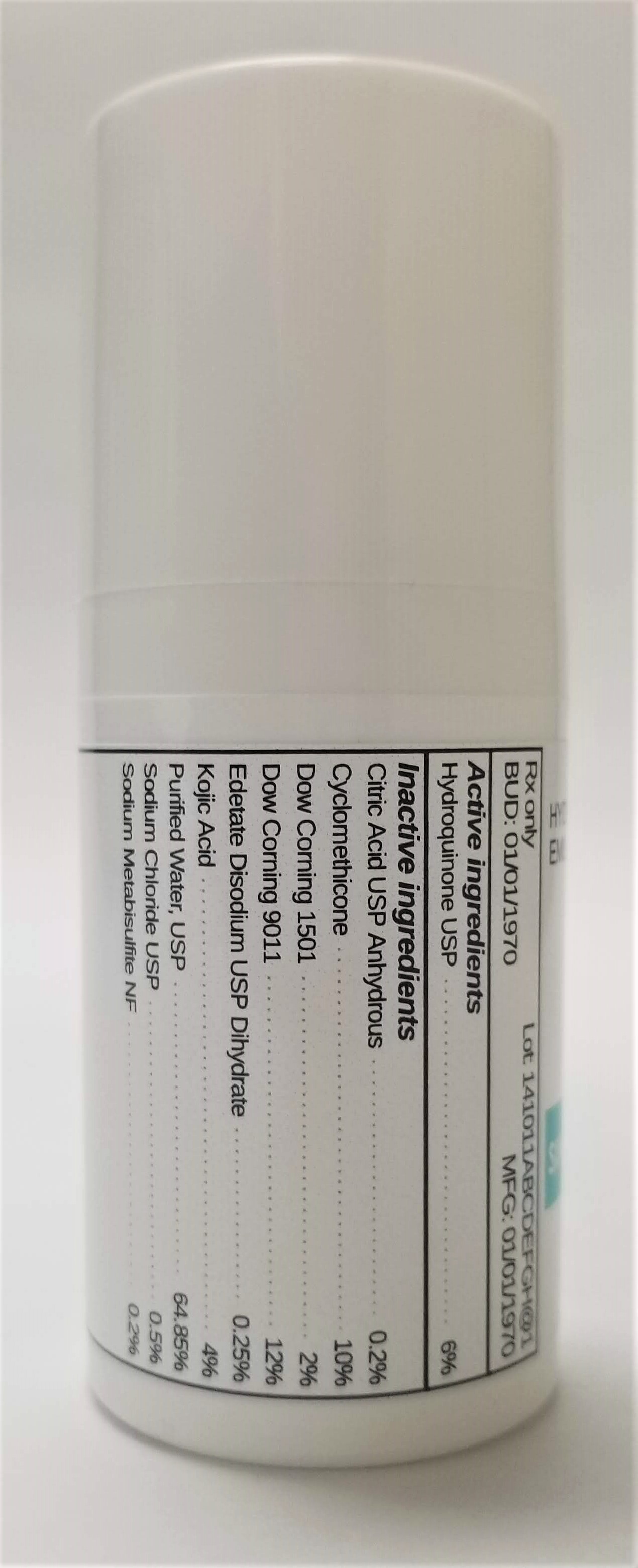 DRUG LABEL: HYDROQUINONE 6%
NDC: 72934-6118 | Form: EMULSION
Manufacturer: Sincerus Florida, LLC
Category: prescription | Type: HUMAN PRESCRIPTION DRUG LABEL
Date: 20190424

ACTIVE INGREDIENTS: HYDROQUINONE 6 g/100 g

HYDROQUINONE 6%